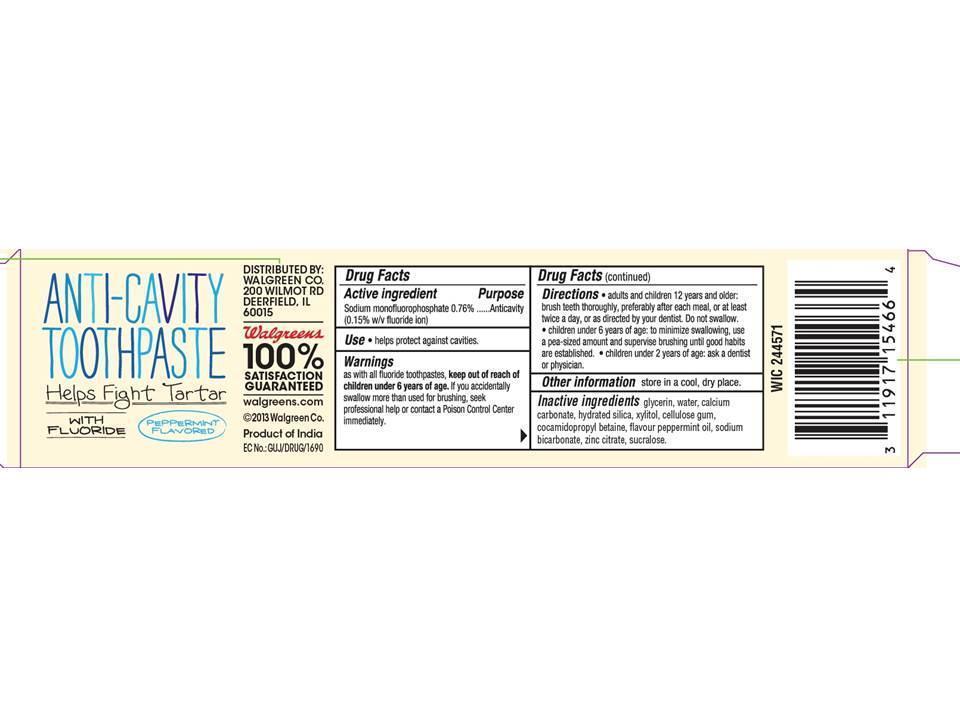 DRUG LABEL: Ology Fluoride
NDC: 0363-2008 | Form: PASTE
Manufacturer: Walgreens
Category: otc | Type: HUMAN OTC DRUG LABEL
Date: 20130321

ACTIVE INGREDIENTS: SODIUM MONOFLUOROPHOSPHATE 7.6 mg/1 g
INACTIVE INGREDIENTS: GLYCERIN; CALCIUM CARBONATE; XYLITOL; COCAMIDOPROPYL BETAINE; HYDRATED SILICA; SODIUM BICARBONATE; ZINC CITRATE; SUCRALOSE

Ology Fluoride Toothpaste

Active Ingredients

Sodium monofluorophosphate 0.76%................Anticavity (0.15% w/v fluoride ion)

USES

- Helps protect against cavitites.

USES

- Helps protect against cavitites.

Directions

- adults and children 12 years and older: brush teeth thoroughly, preferably after each meal, or at least twice a day, or as directed by your dentist. do not swallow.
- children under 6 years of age: to minimize swallowing, use a pea-sized amount and supervise brushing until good habits are established.
- children under 2 years of age: ask a dentist or physician.

Inactive ingredients

glycerin, water, calcium carbonate, hydrated silica, xylitol, cellulose gum, cocamidopropyl betaine, flavour peppermint oil, sodium bicarbonate, zinc citrate, sucralose.

Warnings

as with all fluoride toothpastes, keep out of reach of children under 6 years of age. If you accidentally swallow more than used for brushing, seek professional help or contact a Poison Control Center immediately.

keep out of reach of children under 6 years of age.